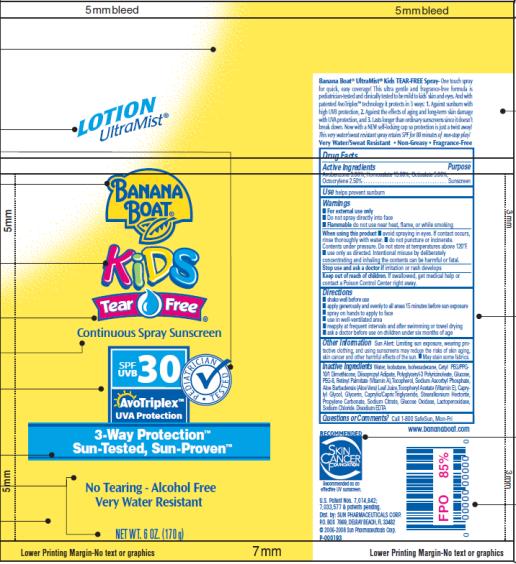 DRUG LABEL: Banana Boat Kids UltraMist Tear Free SPF 30
NDC: 17630-2011 | Form: SPRAY
Manufacturer: Accra-Pac, Inc.
Category: otc | Type: HUMAN OTC DRUG LABEL
Date: 20100325

ACTIVE INGREDIENTS: AVOBENZONE 0.03 g/1 g; HOMOSALATE 0.15 g/1 g; OCTISALATE 0.05 g/1 g; OCTOCRYLENE 0.025 g/1 g
INACTIVE INGREDIENTS: WATER; ISOBUTANE; DIISOPROPYL ADIPATE; VITAMIN A PALMITATE; SODIUM ASCORBYL PHOSPHATE; ALOE VERA LEAF; .ALPHA.-TOCOPHEROL ACETATE, D-; CAPRYLYL GLYCOL; GLYCERIN; MEDIUM-CHAIN TRIGLYCERIDES; PROPYLENE CARBONATE; SODIUM CITRATE; EDETATE DISODIUM

Banana Boat Kids UltraMist Tear Free SPF 30

Drug Facts

Active Ingredients

Avobenzone 0.03g / 1g

Homosalate 0.15g / 1g

Octisalate 0.05g / 1g

Octocrylene 0.025g / 1g

Purpose

Sunscreen

Use

helps prevent sunburn

Warnings

- For external use only
- Do not spray directly into face
- Flammable do not use near heat, flame, or while smoking

When using this product

- avoid spraying in eyes. If contact occurs, rinse thoroughly with water.
- do not puncture or incinerate. Contents under pressure. Do not store at temperatures above 120°F.
- use only as directed. Intentional misuse by deliberately concentrating and inhaling the contents can be harmful or fatal.

Stop use and ask a doctor if

irritation or rash develops

Keep out of reach of children.

If swallowed, get medical help or contact a Poison Control Center right away.

Directions

- shake well before use
- apply generously and evenly to all areas 15 minutes before sun exposure
- spray on hands to apply to face
- use in well-ventilated area
- reapply at frequent intervals and after swimming or towel drying
- ask a doctor before use on children under six months of age

Other Information

Sun Alert: Limiting sun exposure, wearing protective clothing, and using sunscreens may reduce the risks of skin aging, skin cancer and other harmful effects of the sun.

- May stain some fabrics.

Inactive Ingredients

Water, Isobutane, Isohexadecane, Cetyl PEG/PPG-10/1 Dimethicone, Diisopropyl Adipate, Polyglyceryl-3 Polyricinoleate, Glucose, PEG-8, Retinyl Palmitate (Vitamin A), Tocopherol, Sodium Ascorbyl Phosphate, Aloe Barbadensis (Aloe Vera) Leaf Juice, Tocopheryl Acetate (Vitamin E), Caprylyl Glycol, Glycerin, Caprylic/Capric Triglyceride, Stearalkonium Hectorite, Propylene Carbonate, Sodium Citrate, Glucose Oxidase, Lactoperoxidase, Sodium Chloride, Disodium EDTA

Questions or Comments?

Call 1-800 SafeSun, Mon-Fri

Dist. by: SUN PHARMACEUTICALS CORP.
P.O. BOX 7869, DELRAY BEACH, FL 33482
www.bananaboat.com

PRINCIPAL DISPLAY PANEL

LOTION
ULTRAMIST®
BANANA
BOAT®
KIDS
TEAR FREE®
Continuous Spray Sunscreen
SPF/UVB 30
PEDIATRICIAN TESTED
AvoTriplex TM
UVA Protection
3-Way Protection TM
Sun-Tested, Sun-Proven TM
No Tearing – Alcohol Free
Very Water Resistant
NET WT. 6 OZ. (170g)